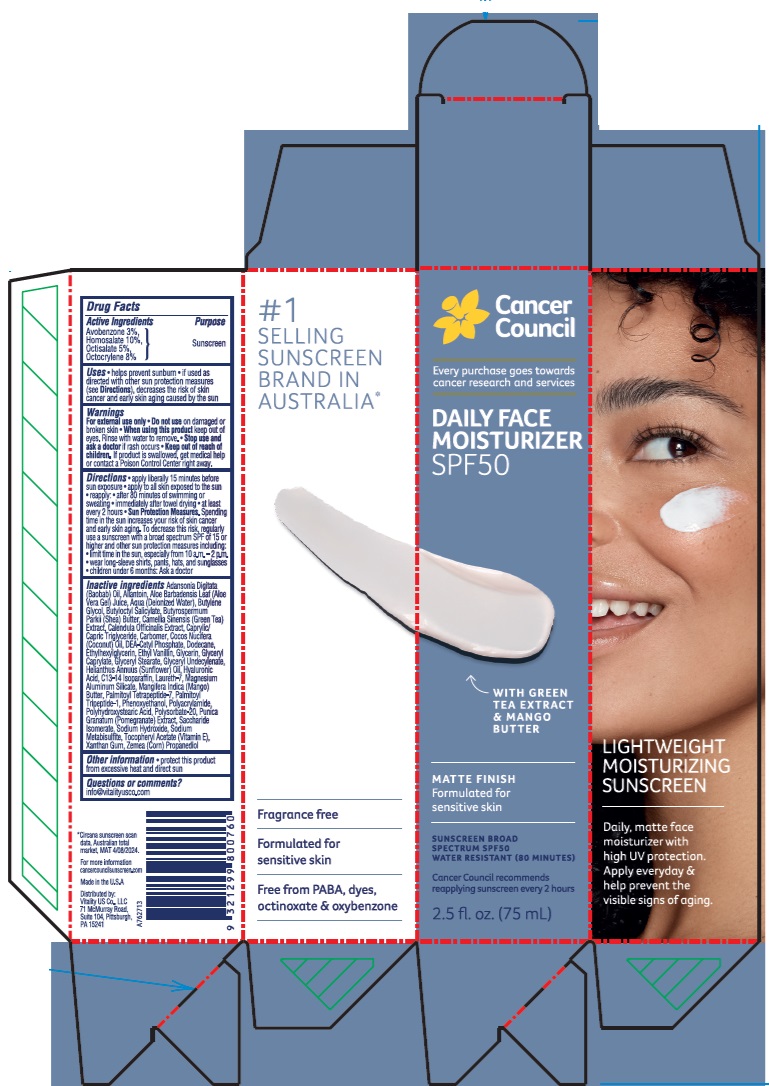 DRUG LABEL: Cancer Council Daily Face Moisturizer SPF50
NDC: 84258-005 | Form: LOTION
Manufacturer: Vitality US Co.
Category: otc | Type: HUMAN OTC DRUG LABEL
Date: 20240619

ACTIVE INGREDIENTS: HOMOSALATE 100 mg/1 mL; OCTOCRYLENE 80 mg/1 mL; AVOBENZONE 30 mg/1 mL; OCTISALATE 50 mg/1 mL
INACTIVE INGREDIENTS: GLYCERYL MONOSTEARATE; MANGIFERA INDICA SEED BUTTER; POLYACRYLAMIDE (1500 MW); GLYCERIN; ETHYL VANILLIN; DODECANE; C13-14 ISOPARAFFIN; PALMITOYL TETRAPEPTIDE-7; DIETHANOLAMINE CETYL PHOSPHATE; MAGNESIUM ALUMINUM SILICATE; ETHYLHEXYLGLYCERIN; SUNFLOWER OIL; LAURETH-7; PALMITOYL TRIPEPTIDE-1; SACCHARIDE ISOMERATE; SODIUM METABISULFITE; PROPANEDIOL; .ALPHA.-TOCOPHEROL ACETATE; ADANSONIA DIGITATA SEED OIL; ALLANTOIN; BUTYLENE GLYCOL; SHEA BUTTER; BUTYLOCTYL SALICYLATE; WATER; GREEN TEA LEAF; ALOE VERA LEAF; CALENDULA OFFICINALIS FLOWER; MEDIUM-CHAIN TRIGLYCERIDES; COCONUT OIL; GLYCERYL CAPRYLATE; GLYCERYL 1-UNDECYLENATE; HYALURONIC ACID; PHENOXYETHANOL; POLYSORBATE 20; POLYHYDROXYSTEARIC ACID (2300 MW); SODIUM HYDROXIDE; PUNICA GRANATUM ROOT BARK; XANTHAN GUM; CARBOMER HOMOPOLYMER, UNSPECIFIED TYPE

Cancer Council Daily Face Moisturizer SPF50

Active Ingredients

Avobenzone 3%

Homosalate 10%

Octisalate 5%

Octocrylene 8%

Purpose

Sunscreen

Uses

- helps prevent sunburn
- if used as directed with other sun protection measures (see Directions), decreases the risk of skin cancer and early skin aging caused by the sun

Warnings

For external use only

Do not use

on damaged or broken skin

When using this product

keep out of eyes. Rinse with water to remove.

Stop use and ask a doctor

if rash occurs

Keep out of reach of children.

If product is swallowed, get medical help or contact a Poison Control Center right away.

Directions

- apply liberally 15 minutes before sun exposure
- apply to all skin exposed to the sun
- reapply:
- after 80 minutes of swimming or sweating
- immediately after towel drying
- at least every 2 hours
- Sun Protection Measures. Spending time in the sun increases your risk of skin cancer and early skin aging. To decrease this risk, regularly use a sunscreen with a broad spectrum SPF of 15 or higher and other sun protection measures including:
- limit time in the sun, especially from 10 a.m. - 2 p.m.
- wear long-sleeve shirts, pants, hats, and sunglasses
- children under 6 months: Ask a doctor

Inactive ingredients

Adansonia Digitata (Baobab) Oil, Allantoin, Aloe Barbadensis Leaf (Aloe Vera Gel) Juice, Aqua (Deionized Water), Butylene Glycol, Butyloctyl Salicylate, Butyrospermum Parkii (Shea) Butter, Camellia Sinensis (Green Tea) Extract, Calendula Officinalis Extract, Caprylic/Capric Triglyceride, Carbomer, Cocos Nucifera (Coconut) Oil, DEA-Cetyl Phosphate, Dodecane, Ethylhexylglycerin, Ethyl Vanillin, Glycerin, Glyceryl Caprylate, Glyceryl Stearate, Glyceryl Undecylenate, Helianthus Annuus (Sunflower) Oil, Hyaluronic Acid, C13-14 Isoparaffin, Laureth-7, Magnesium Aluminum Silicate, Mangifera Indica (Mango) Butter, Palmitoyl Tetrapeptide-7, Palmitoyl Tripeptide-1, Phenoxyethanol, Polyacrylamide, Polyhydroxystearic Acid, Polysorbate-20, Punica Granatum (Pomegranate) Extract, Saccharide Isomerate, Sodium Hydroxide, Sodium Metabisulfite, Tocopheryl Acetate (Vitamin E), Xanthan Gum, Zemea (Corn) Propanediol

Other information

- protect this product from excessive heat and direct sun

Questions or comments?

info@vitalityusco.com